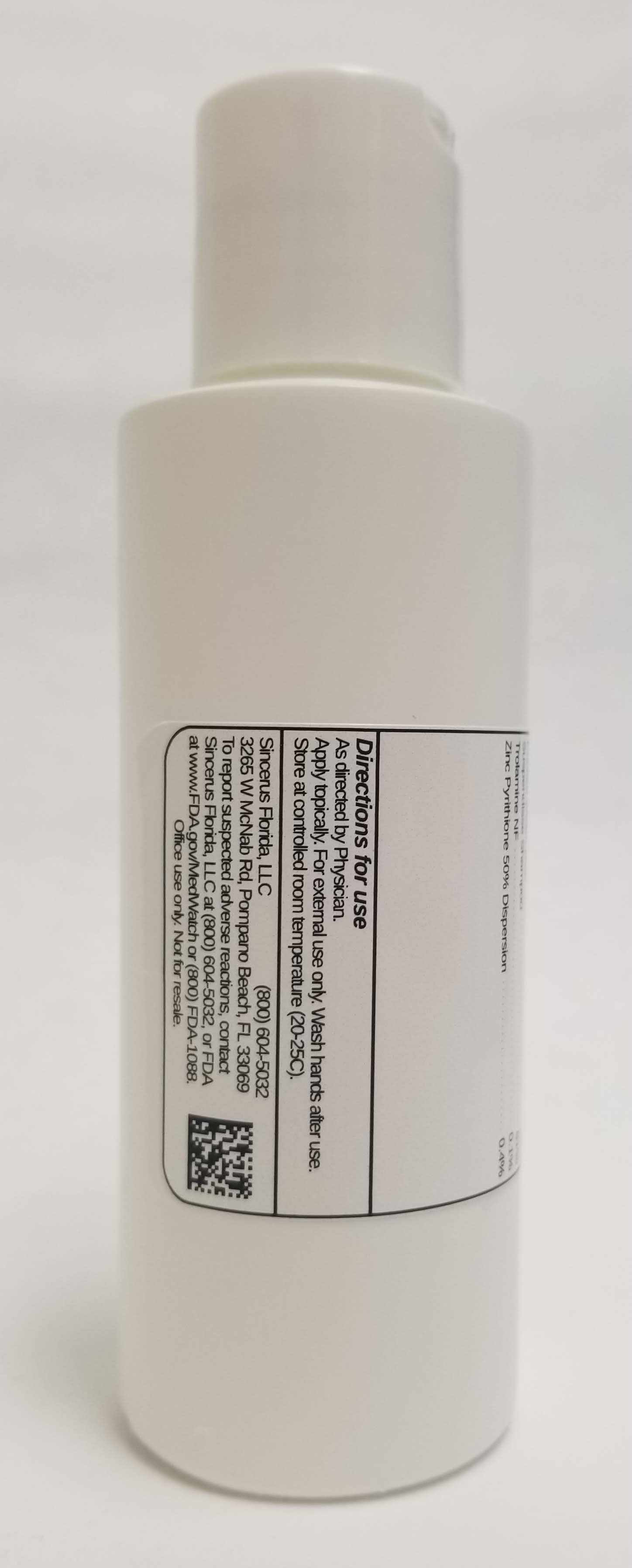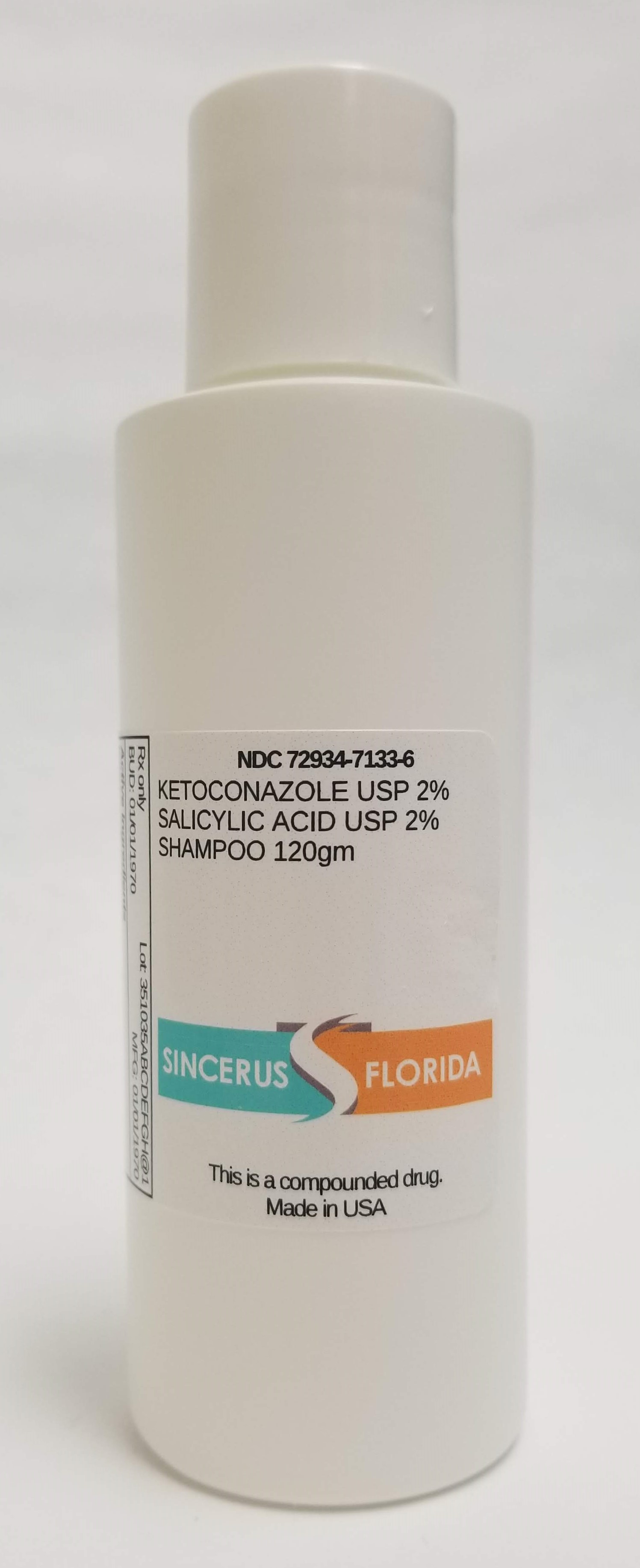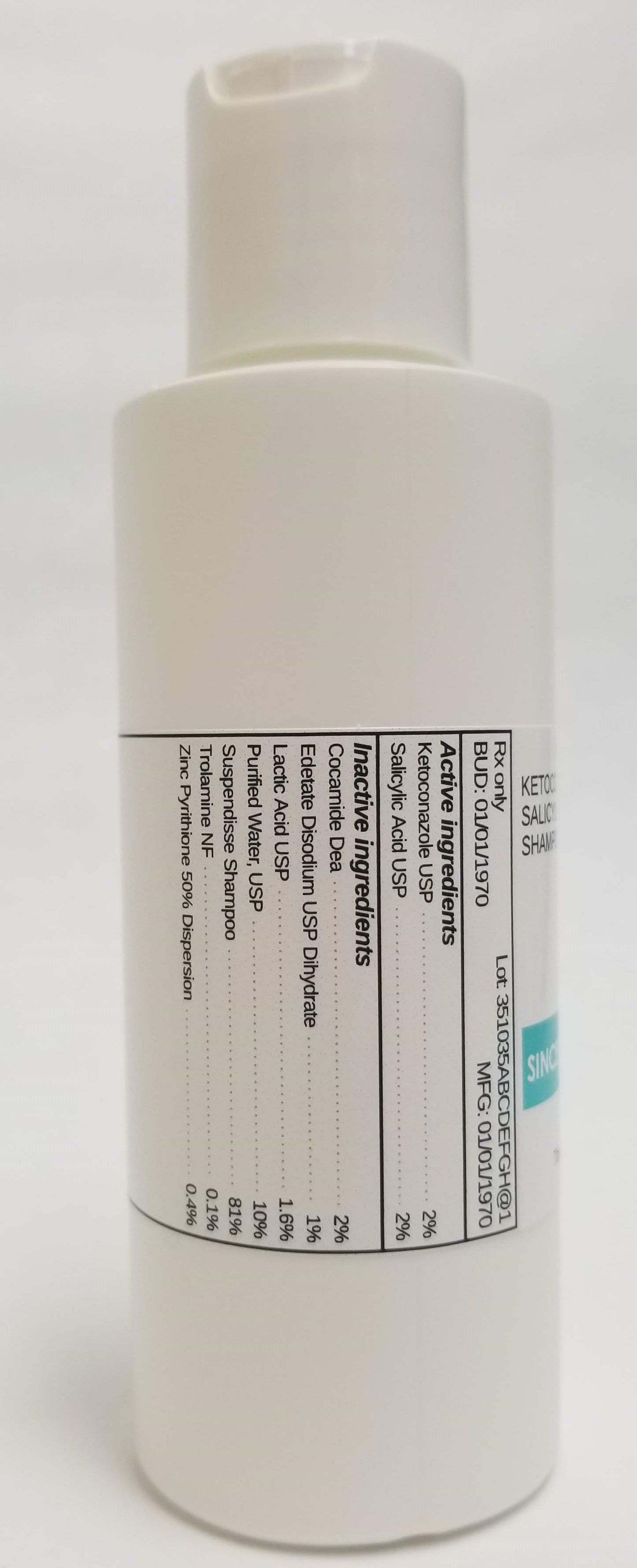 DRUG LABEL: KETOCONAZOLE 2% / SALICYLIC ACID 2%
NDC: 72934-7133 | Form: SHAMPOO
Manufacturer: Sincerus Florida, LLC
Category: prescription | Type: HUMAN PRESCRIPTION DRUG LABEL
Date: 20190516

ACTIVE INGREDIENTS: SALICYLIC ACID 2 g/100 g; KETOCONAZOLE 2 g/100 g

KETOCONAZOLE 2% / SALICYLIC ACID 2%